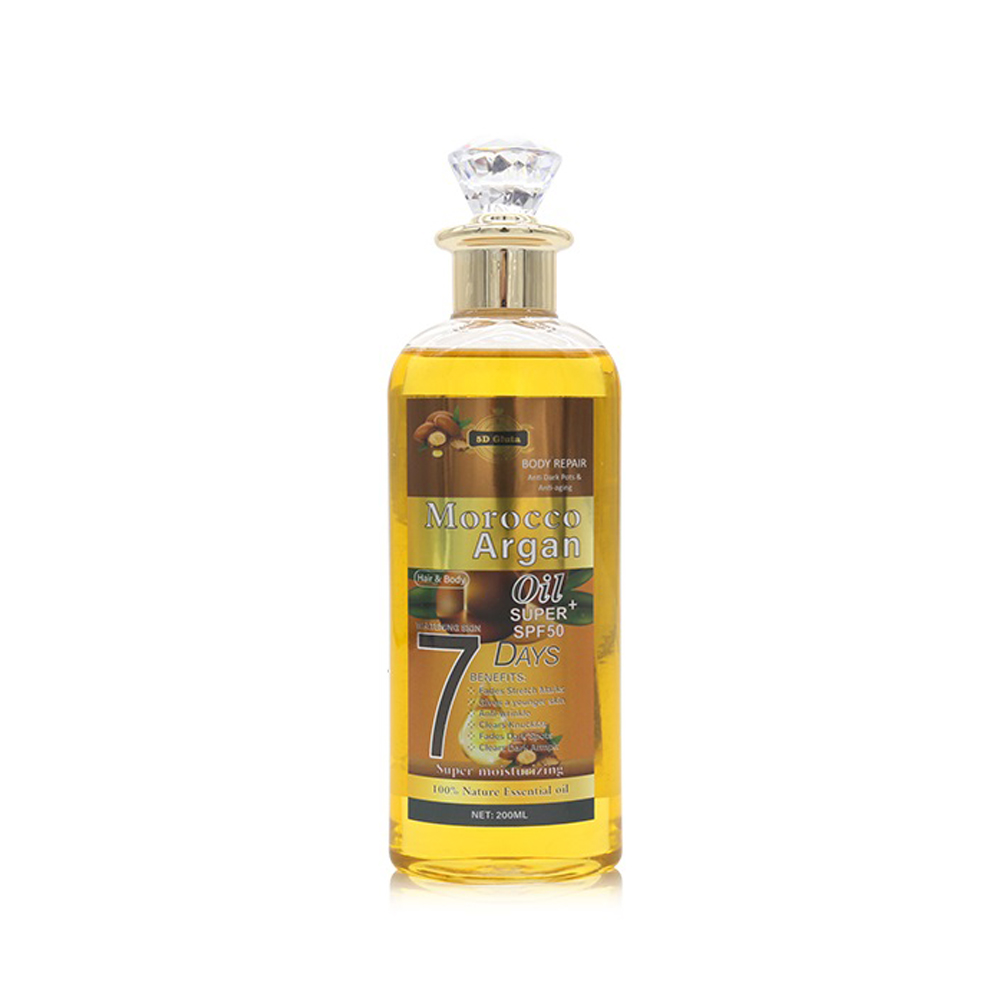 DRUG LABEL: Morocco Argan Oil
NDC: 84423-051 | Form: OIL
Manufacturer: Guangzhou Kadiya Biotechnology Co., Ltd.
Category: otc | Type: HUMAN OTC DRUG LABEL
Date: 20241003

ACTIVE INGREDIENTS: SQUALANE 4 g/200 mL; KOJIC ACID 0.4 g/200 mL; ARGAN OIL 0.6 g/200 mL
INACTIVE INGREDIENTS: MINERAL OIL; DIMETHICONE; ISOPROPYL PALMITATE; JOJOBA OIL; OLIVE OIL; WATER; PHENOXYETHANOL; D&C RED NO. 33; ISOPROPYL MYRISTATE; ETHYLHEXYLGLYCERIN; PROPYLPARABEN; SOLVENT RED 72

PURPOSE

For soothing, moisturising and nourishing the skin.

INACTIVE INGREDIENT

MINERAL OIL，ISOPROPYL MYRISTATE，DIMETHICONE，ISOPROPYL PALMITATE，SIMMONDSIA CHINENSIS (JOJOBA) SEED OIL， PRUNUS AMYGDALUS DULCIS OIL，WATER，PHENOXYETHANOL，ETHYLHEXYLGLYCERIN，PARFUM，PROPYLPARABEN，CI 17200，CI 45370

WARNINGS

1.Before use, perform a skin test on your arm and discontinue use if you have allergy symptoms or skin abnormalities.
2、For external use only, avoid contact with eyes when used
3、Keep out of reach of children

INDICATIONS AND USAGE

Argan essential oil is rich in fatty acids, vitamin E, squalene and sterols. It is a great care product that can moisturize hair, apply to skin and enhance skin metabolism, antioxidant and moisturizingrepair damage skin.

DOSAGE AND ADMINISTRATION

After cleansing, apply 3-5 drops of this product to your hands and gently rub them until they are warm. Gently massage until the essential oil is completely absorbed by your skin.

KEEP OUT OF REACH OF CHILDREN SECTION

ACTIVE INGREDIENT

Kojic acid0.2%
ARGANIA SPINOSA KERNEL OIL0.3%
SQUALANE 2%

PACKAGE LABEL

Active Ingredients
Kojic acid0.2%
ARGANIA SPINOSA KERNEL OIL0.3%
SQUALANE 2%

Uses：
For soothing, moisturising and nourishing the skin.
The storage method：
Store sealed in a cool place and out of sunlight

Warning.
1.Before use, perform a skin test on your arm and discontinue use if you have allergy symptoms or skin abnormalities.
2、For external use only, avoid contact with eyes when used
3、Keep out of reach of children

Inactive ingredients：
MINERAL OIL，ISOPROPYL MYRISTATE，DIMETHICONE，ISOPROPYL PALMITATE，SIMMONDSIA CHINENSIS (JOJOBA) SEED OIL， PRUNUS AMYGDALUS DULCIS OIL，WATER，PHENOXYETHANOL，ETHYLHEXYLGLYCERIN，PARFUM，PROPYLPARABEN，CI 17200，CI 45370